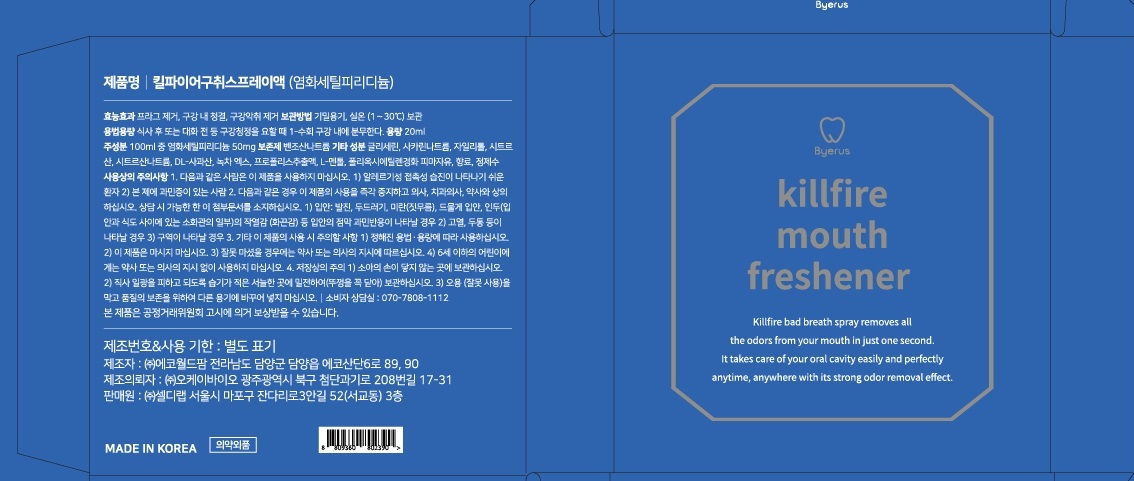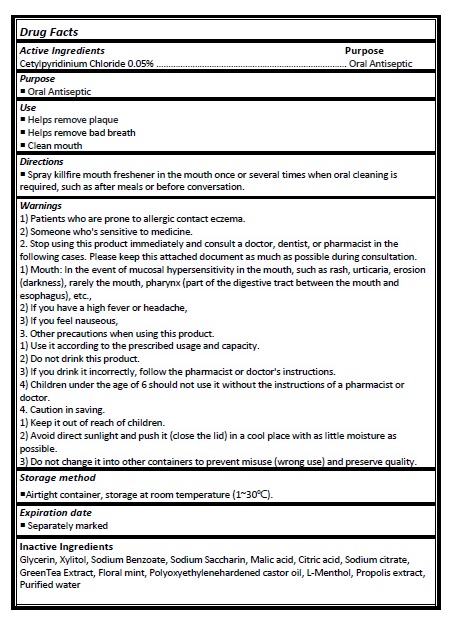 DRUG LABEL: Killfire mouth freshener
NDC: 24765-134 | Form: SPRAY
Manufacturer: Pharmacal-International. Co., Ltd.
Category: otc | Type: HUMAN OTC DRUG LABEL
Date: 20241025

ACTIVE INGREDIENTS: CETYLPYRIDINIUM CHLORIDE 0.05 g/100 mL
INACTIVE INGREDIENTS: GLYCERIN; XYLITOL; CITRIC ACID MONOHYDRATE; MALIC ACID; SODIUM BENZOATE; SODIUM CITRATE; SACCHARIN SODIUM; GREEN TEA LEAF; RACEMENTHOL; WATER; PROPOLIS WAX; POLYOXYL 35 CASTOR OIL

Active ingredient

Cetylpyridinium Chloride 0.05%

Purpose

Oral Antiseptic

Use

- Helps remove plaque
- Helps remove bad breath
- Clean mouth

Directions

- Spray killfire mouth freshener in the mouth once or several times when oral cleaning is required, such as after meals or before conversation.

Warnings

1) Patients who are prone to allergic contact eczema.

2) Someone who's sensitive to medicine.

2. Stop using this product immediately and consult a doctor, dentist, or pharmacist in the following cases. Please keep this attached document as much as possible during consultation. 1) Mouth: In the event of mucosal hypersensitivity in the mouth, such as rash, urticaria, erosion (darkness), rarely the mouth, pharynx (part of the digestive tract between the mouth and esophagus), etc.,

2) If you have a high fever or headache,

3) If you feel nauseous,

3. Other precautions when using this product.

1) Use it according to the prescribed usage and capacity.

2) Do not drink this product.

3) If you drink it incorrectly, follow the pharmacist or doctor's instructions.

4) Children under the age of 6 should not use it without the instructions of a pharmacist or doctor.

4. Caution in saving.

1) Keep it out of reach of children.

2) Avoid direct sunlight and push it (close the lid) in a cool place with as little moisture as possible.

3) Do not change it into other containers to prevent misuse (wrong use) and preserve quality.

Storage method

Airtight container, storage at room temperature (1~30℃).

Expiration date

Separately marked

Inactive Ingredients

Glycerin, Xylitol, Sodium Benzoate, Sodium Saccharin, Malic acid, Citric acid, Sodium citrate,
GreenTea Extract, Floral mint, Polyoxyethylenehardened castor oil, L-Menthol, Propolis extract,
Purified water